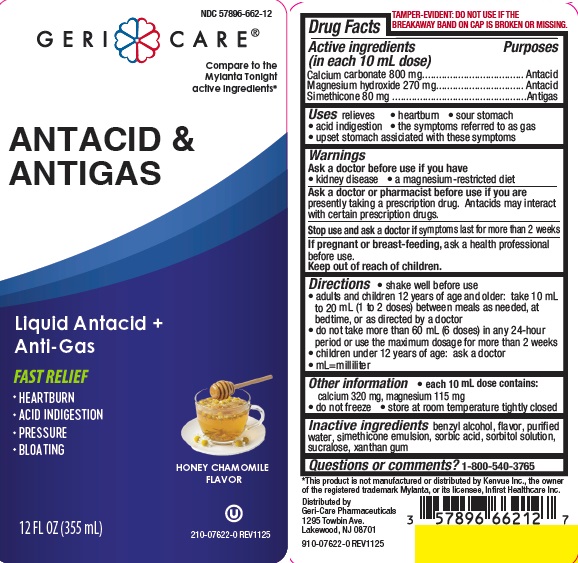 DRUG LABEL: ANTACID AND ANTIGAS
NDC: 57896-662 | Form: LIQUID
Manufacturer: Geri-Care Pharmaceuticals, Corp
Category: otc | Type: HUMAN OTC DRUG LABEL
Date: 20251230

ACTIVE INGREDIENTS: CALCIUM CARBONATE 800 mg/10 mL; DIMETHICONE 80 mg/10 mL; MAGNESIUM HYDROXIDE 270 mg/10 mL
INACTIVE INGREDIENTS: BENZYL ALCOHOL; SORBIC ACID; SUCRALOSE; XANTHAN GUM; WATER; SORBITOL SOLUTION

gc 662 mylanta honey

Active ingredients (in each 10 mL dose)

Calcium carbonate 800 mg
Magnesium hydroxide 270 mg
Simethicone 80 mg

Purposes

Antacid

Antigas

Uses

relieves

- heartburn
- sour stomach
- acid indigestion
- the symptoms referred to as gas
- upset stomach assiciated with these symptoms

Warnings

Ask a doctor before use if you have

- kidney disease
- a magnesium-restricted diet

Ask a doctor or pharmacist before use if you are

presently taking a prescription drug.
Antacids may interact with certain prescription drugs.

Stop use and ask a doctor if symptoms last for more than 2 weeks

If pregnant or breast-feeding,

ask a health professional before use.

Keep out of reach of children.

Directions

- shake well before use
- adults and children 12 years of age and older: take 10 mL to 20 mL (1 to 2 doses) between meals as needed, at bedtime,

or as directed by a doctor

- do not take more than 60 mL (6 doses) in any 24-hour period or use the maximum dosage for more than 2 weeks
- children under 12 years of age: ask a doctor
- mL = milliliter

Other information

- each 10 mL dose contains: calcium 320 mg, magnesium 115 mg
- do not freeze
- store at room temperature tightly closed

Inactive ingredients

benzyl alcohol, flavor, purified water, simethicone emulsion, sorbic acid, sorbitol solution, sucralose, xanthan gum

Questions or comments?

1-800-540-3765